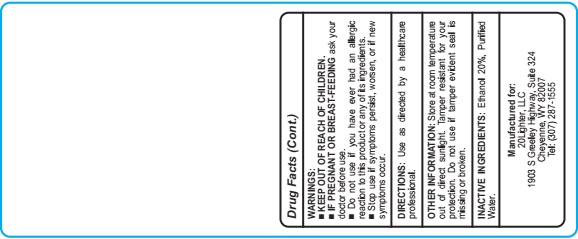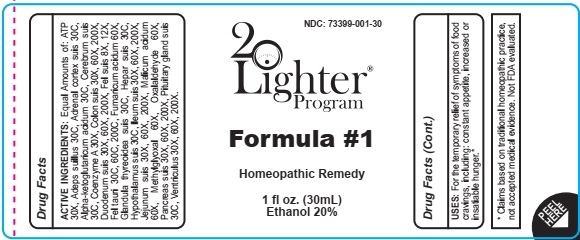 DRUG LABEL: Formula 1
NDC: 73399-001 | Form: LIQUID
Manufacturer: 20Lighter, LLC.
Category: homeopathic | Type: HUMAN OTC DRUG LABEL
Date: 20211115

ACTIVE INGREDIENTS: ADENOSINE TRIPHOSPHATE 30 [hp_X]/30 mL; LARD 30 [hp_C]/30 mL; SUS SCROFA CEREBRUM 30 [hp_C]/30 mL; COENZYME A 30 [hp_X]/30 mL; SUS SCROFA COLON 30 [hp_X]/30 mL; SUS SCROFA DUODENUM 30 [hp_X]/30 mL; BOS TAURUS BILE 30 [hp_C]/30 mL; FUMARIC ACID 60 [hp_X]/30 mL; THYROID, PORCINE 30 [hp_C]/30 mL; PORK LIVER 30 [hp_C]/30 mL; BOS TAURUS HYPOTHALAMUS 30 [hp_C]/30 mL; PYRUVALDEHYDE 60 [hp_X]/30 mL; GLYOXAL 60 [hp_X]/30 mL; SUS SCROFA PANCREAS 30 [hp_X]/30 mL
INACTIVE INGREDIENTS: ALCOHOL; WATER

Formula 1

ACTIVE INGREDIENT

ACTIVE INGREDIENTS: Equal Amounts of: ATP 30X, Adeps suillus 30C, Adrenal cortex suis 30C, Alpha-ketoglutaricum acidum 30C, Cerebrum suis 30C, Coenzyme A 30X, Colon suis 30X, 60X, 200X, Duodenum suis 30X, 60X, 200X, Fel suis 8X, 12X, Fel tauri 30C, 60C, 200C, Fumaricum acidum 60X, Glandula thyreoidea suis 30C, Hepar suis 30C, Hypothalamus suis 30C, Ileum suis 30X, 60X, 200X, Jejunum suis 30X, 60X, 200X, Malicum acidum 60X, Methylglyoxal 60X, Oxalaldehyde 60X, Pancreas suis 30X, 60X, 200X, Pituitary gland suis 30C, Ventriculus 30X, 60X, 200X.

* Claims based on traditional homeopathic practice, not accepted medical evidence. Not FDA evaluated.

INDICATIONS AND USAGE

USES: For the temporary relief of symptoms of food cravings, including: constant appetite, increased or insatiable hunger.*

WARNINGS:
▀ KEEP OUT OF REACH OF CHILDREN.
▀ IF PREGNANT OR BREAST-FEEDING ask your
doctor before use.
▀ Do not use if you have ever had an allergic
reaction to this product or any of its ingredients.
▀ Stop use if symptoms persist, worsen, or if new
symptoms occur.

▀ KEEP OUT OF REACH OF CHILDREN.

DOSAGE AND ADMINISTRATION

DIRECTIONS: Use as directed by a healthcare professional.

OTHER INFORMATION: Store at room temperature out of direct sunlight. Tamper resistant for your protection. Do not use if tamper evident seal is missing or broken.

INACTIVE INGREDIENTS: Ethanol 20%, Purified Water.

QUESTIONS

Manufactured for:
20Lighter, LLC
1903 S Greeley Highway, Suite 324
Cheyenne, WY 82007
Tel: (307) 287-1555

PACKAGE LABEL

NDC: 73399-001-30

20Lighter Program

Formula #1

Homeopathic Remedy

1 fl oz. (30mL)

Ethanol 20%

PURPOSE

For the temporary relief of symptoms of food cravings, including: constant appetite, increased or insatiable hunger.*